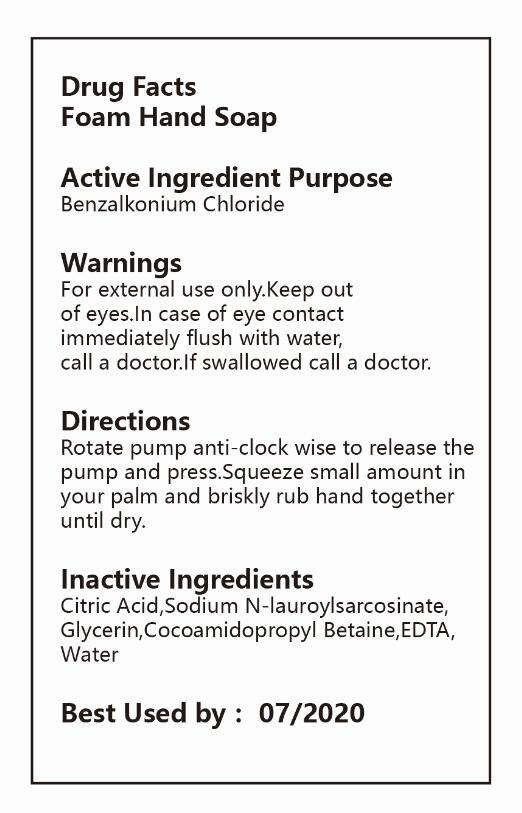 DRUG LABEL: Foam Hand Washing
NDC: 47993-205 | Form: LIQUID
Manufacturer: NINGBO JIANGBEI OCEAN STAR TRADING CO.,LTD
Category: otc | Type: HUMAN OTC DRUG LABEL
Date: 20171206

ACTIVE INGREDIENTS: BENZALKONIUM CHLORIDE 2 g/100 g
INACTIVE INGREDIENTS: CITRIC ACID MONOHYDRATE 0.3 1/100 g; SODIUM LAURYL SARCOSINATE 4 g/100 g; GLYCERIN 5 g/100 g; COCAMIDOPROPYL BETAINE 6 g/100 g; EDETIC ACID 0.5 g/100 g; WATER 82.2 1/100 g

Active Ingredients

Active ingredients--------------purpose

Benzalkonium Chloride

Uses:
Reduces bacteria on the skin. Recommended for repeated use.

Warnings:

For external use only.Keep out of eyes.In case of eye contact immediately flush with water,call a doctor.If swallowed call a doctor.

Directions:

Rotate pump anti-clock wise to release the pump and press.Squeeze small amount in your palm and briskly rub hand together until dry.

Other Information

Do not store above 110F(43C) May discolor certain fabric or surfaces. Harmful to wood finishes and plastics.

KEEP OUT OF REACH OF CHILDREN

Children under 6 years of age should be super vised when using this product.

Inactive Ingredients:

Citric Acid,Sodium N-lauroylsarcosinate,Glycerin,Cocoamidopropyl Betaine,EDTA,Water